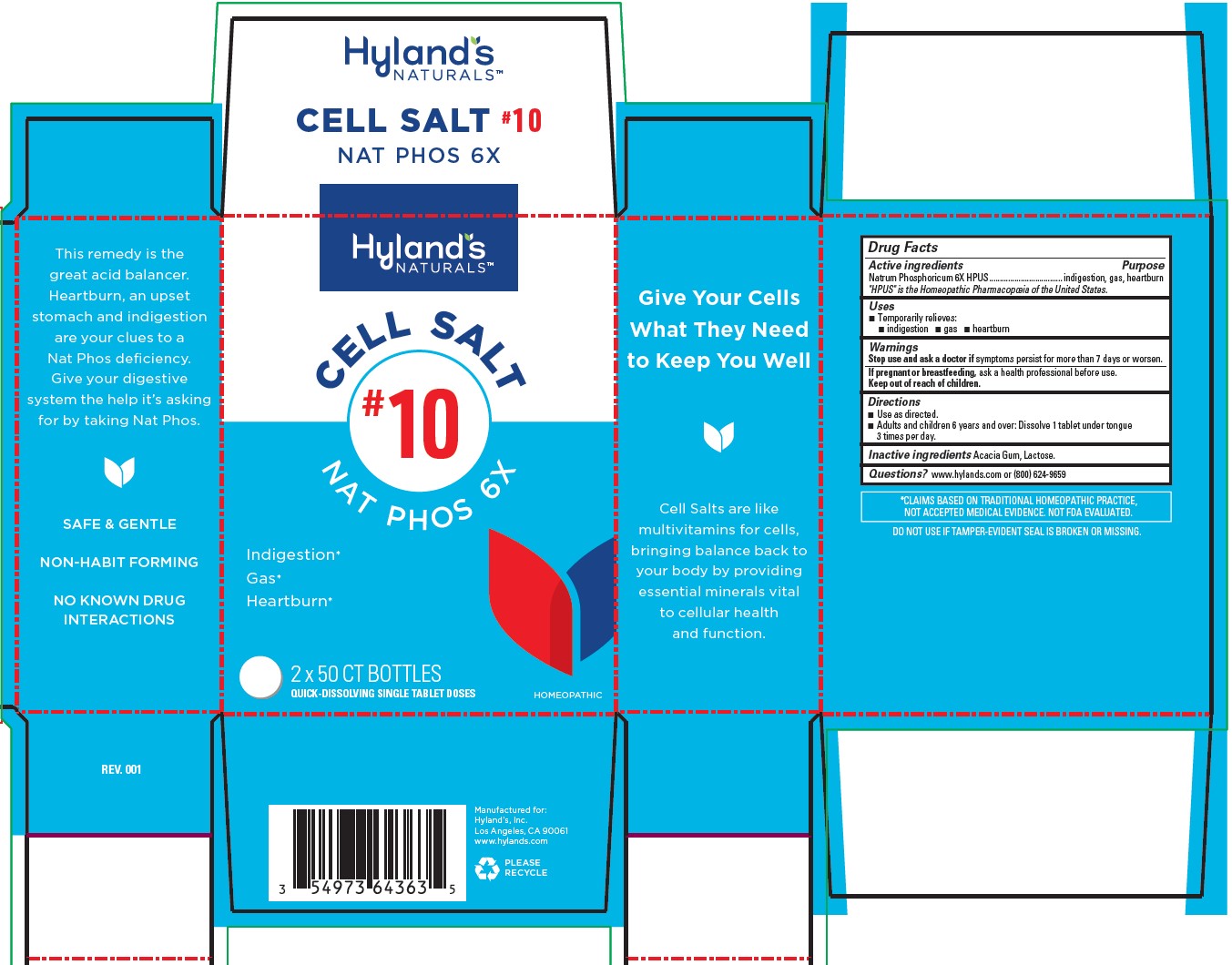 DRUG LABEL: Nat Phos
NDC: 54973-4081 | Form: TABLET
Manufacturer: Hyland's Inc.
Category: homeopathic | Type: HUMAN OTC DRUG LABEL
Date: 20221213

ACTIVE INGREDIENTS: SODIUM PHOSPHATE, DIBASIC, HEPTAHYDRATE 6 [hp_X]/1 1
INACTIVE INGREDIENTS: ACACIA; LACTOSE MONOHYDRATE

Cell Salt #10 Nat Phos 6X

PURPOSE

Temporarily relieves indigestion, gas, heartburn

Drug Facts

Active ingredients

Active ingredients | Purpose
Natrum Phosphoricum 6X HPUS | indigestion, gas, heartburn

"HPUS" is the Homeopathic Pharmacopoeia of the United States.

Uses

■Temporarily relieves:
■ indigestion ■ gas ■ heartburn

Warnings

Stop use and ask a doctor if

symptoms persist for more than 7 days or worsen.

If pregnant or breastfeeding

ask a health professional before use.

Directions

■ Use as directed.
■ Adults and children 6 years and over: Dissolve 1 tablet under tongue 3 times per day.

Inactive ingredients

Acacia Gum, Lactose.

Questions?

www.hylands.com or (800) 624-9659

PACKAGE LABEL - 2 x 50 TABLET BOTTLE CARTON

Hyland's

NATURALS™

CELL SALT

#10

NAT PHOS 6X

Indigestion*

Gas*

Heartburn*

2 x 50 CT BOTTLES

QUICK-DISSOLVING SINGLE TABLETS DOSES

HOMEOPATHIC